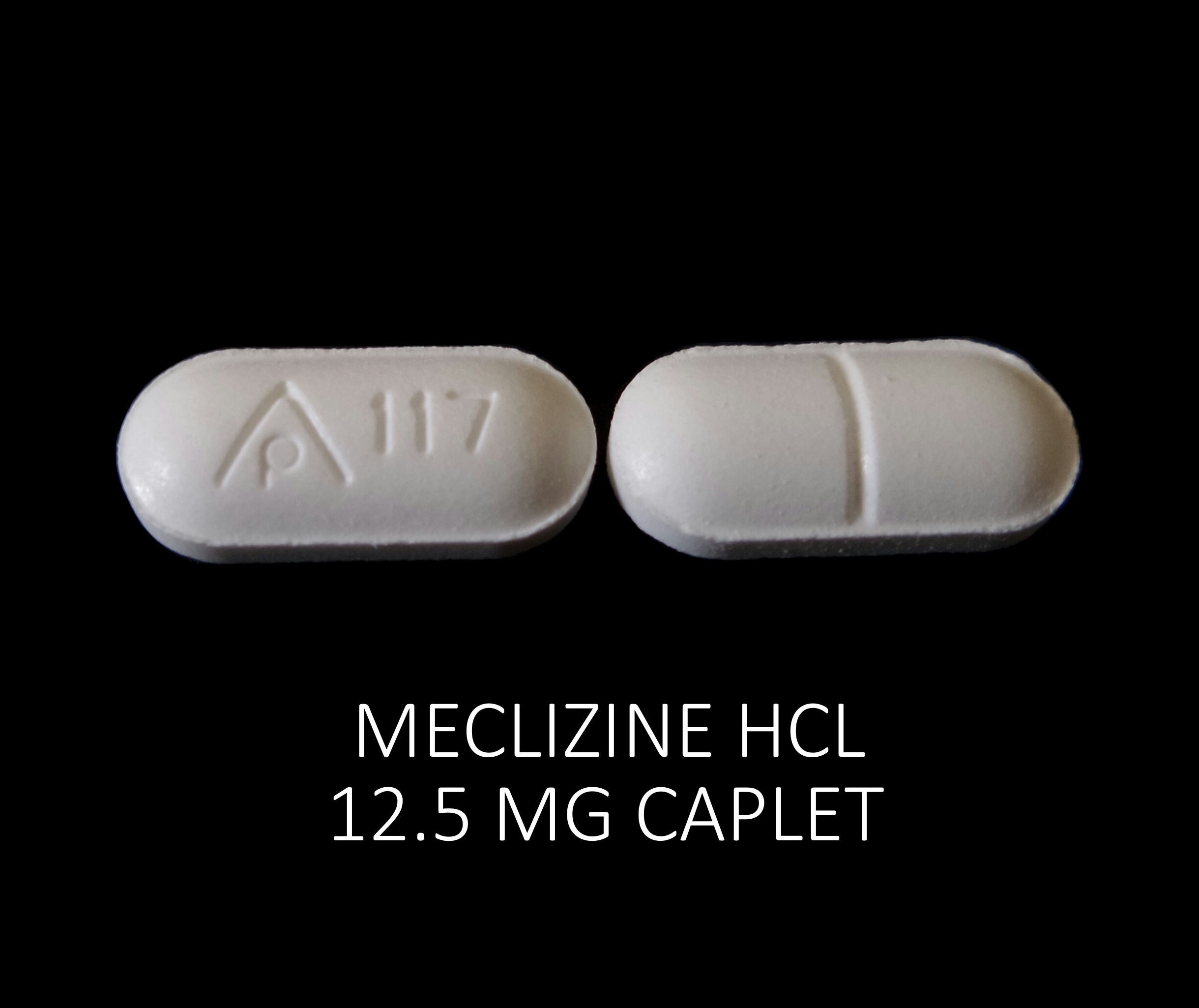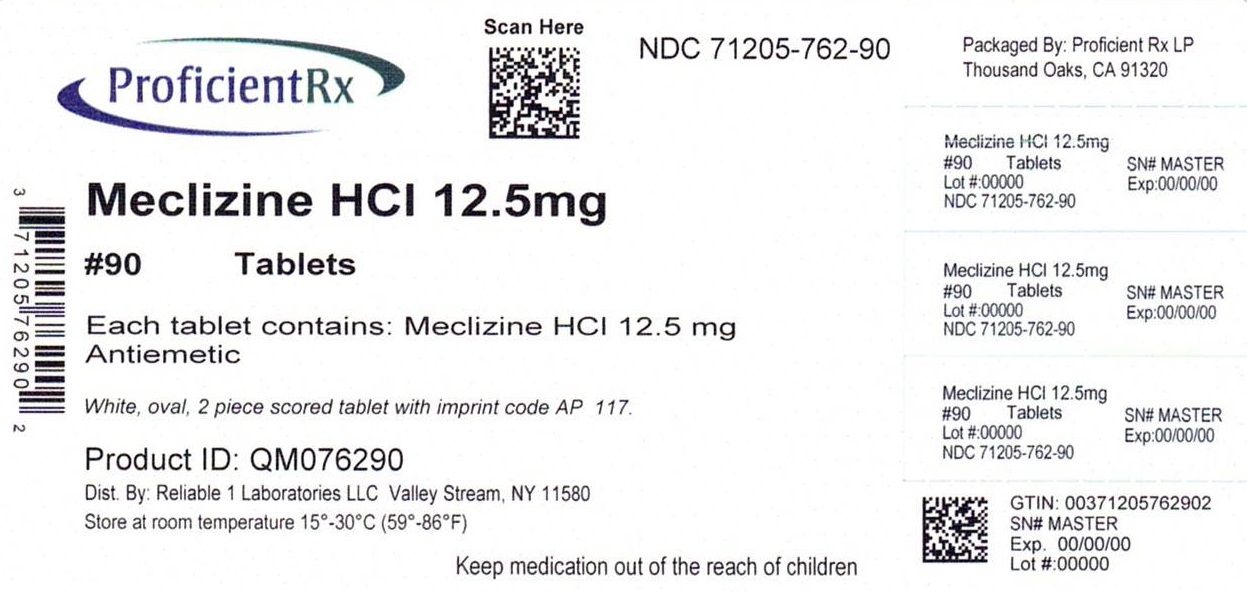 DRUG LABEL: Meclizine HCL 12.5 mg
NDC: 71205-762 | Form: TABLET
Manufacturer: Proficient Rx LP
Category: otc | Type: HUMAN OTC DRUG LABEL
Date: 20251001

ACTIVE INGREDIENTS: MECLIZINE HYDROCHLORIDE 12.5 mg/1 1
INACTIVE INGREDIENTS: SILICON DIOXIDE; CROSCARMELLOSE SODIUM; MAGNESIUM STEARATE; STEARIC ACID; MICROCRYSTALLINE CELLULOSE; ANHYDROUS DIBASIC CALCIUM PHOSPHATE

Meclizine HCL 12.5

Active ingredient (in each caplet)

Meclizine HCL 12.5 mg

Purpose

Antiemetic

Uses

- prevents and treats nausea, vomiting, or dizziness due to motion sickness
- for other uses, consult your doctor

Warnings

Ask a docotor before use if you have

- glaucoma
- a breathing problem such as emphysema or chronic bronchitis
- trouble urinating due to an enlarged prostate gland

Ask a doctor or pharmacist before use if you are taking sedatives or tranquilizers

When using this product

- you may get drowsy
- avoid alcoholic drinks
- alcohol, sedatives and tranquilizers may increase drowsiness
- be careful when driving a motor vehicle or operating machinery

If pregnant or breast-feeding, ask a health professional before use.

Keep out of reach of children. In case of overdose, get medical help or contact a Poison Control Center right away.

Ask a doctor before use if you have

- glaucoma
- a breathing problem such as emphysema or chronic bronchitis
- trouble urinating due to an enlarged prostate gland

Ask a doctor or pharmacist before use if you are taking sedatives or tranquilizers

When using this product

- you may get drowsy
- avoid alcoholic drinks
- alcohol, sedatives and tranquilizers may increase drowsiness
- be careful when driving a motor vehicle or operating machinery

PREGNANCY OR BREAST FEEDING

If pregnant or breast-feeding, ask a health professional before use.

Keep out of reach of children. In case of overdose, get medical help or contact a Poison Control Center right away.

Directions

- adults & children 12 years and over: 2-4 caplets once daily
- children under 12 years: ask a doctor

Other information

- each caplet contains: calcium 51 mg
- store at room temperature 15º-30ºC (59º-86ºF)
- This is a bulk package. Dispense contents with a child-resistant closure in a tight, light-resistant container as defined in the USP.

Inactive ingredients

croscarmellose sodium, dicalcium phosphate, magnesium stearate, microcrystalline cellulose, silicon dioxide, stearic acid

Questions or comments?

call 516-341-0666, 8:30 am - 4:30 pm ET, Monday - Friday

TAMPER EVIDENT: DO NOT USE IF IMPRINTED SAFETY SEAL UNDER CAP IS BROKEN OR MISSING

Distributed by: Reliable 1 Laboratories LLC, Valley Stream, NY 11580

Repackaged by: Proficient Rx LP Thousand Oaks, CA 91320

www.reliable1labs.com

PACKAGE LABEL

NDC 71205-762-90

Meclizine HCL 12.5 mg

ANTIEMETIC

90 CAPLETS

THIS PACKAGE FOR HOUSEHOLDS WITHOUT YOUNG CHILDREN